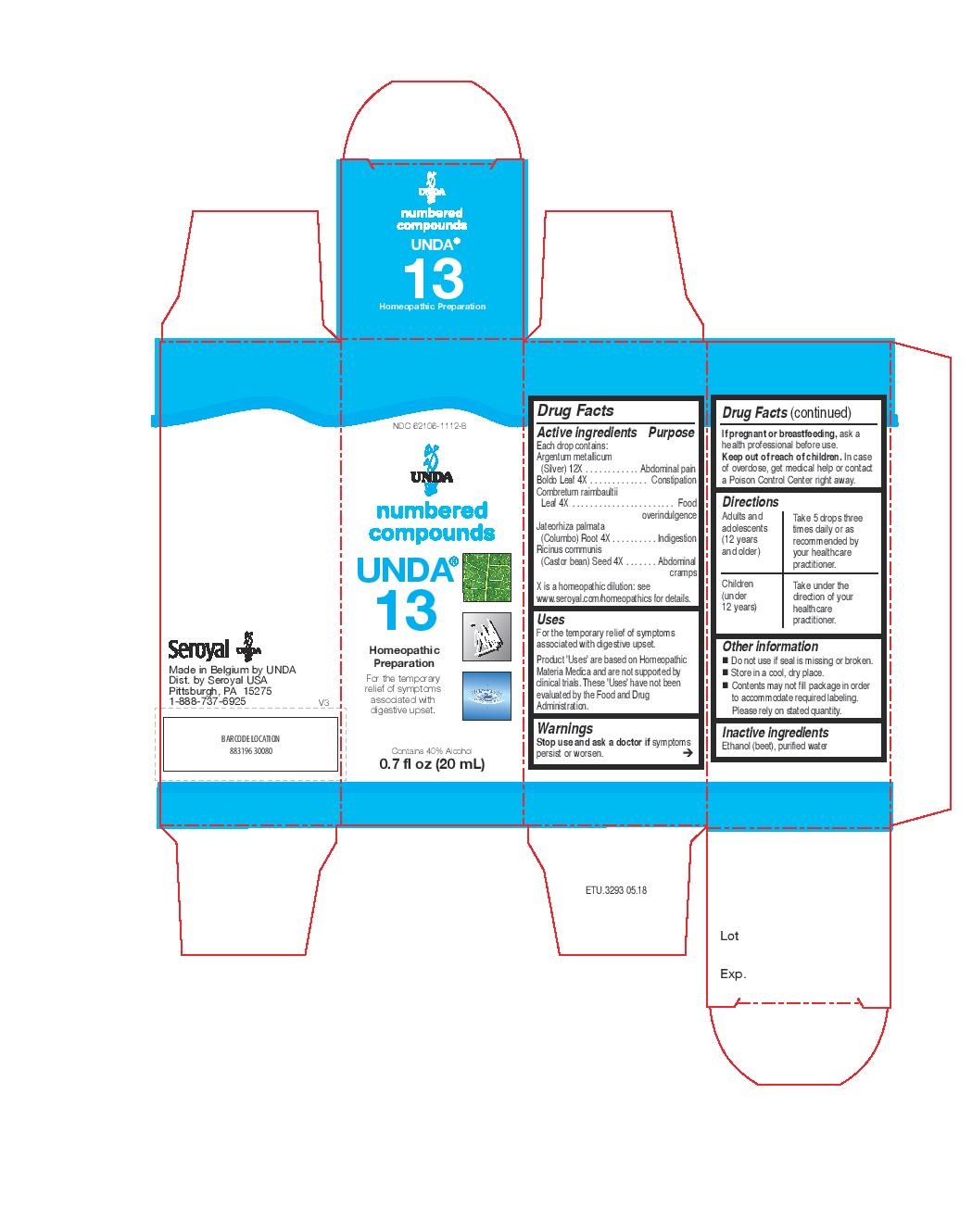 DRUG LABEL: Unda 13
NDC: 62106-1112 | Form: LIQUID
Manufacturer: Seroyal USA
Category: homeopathic | Type: HUMAN OTC DRUG LABEL
Date: 20221108

ACTIVE INGREDIENTS: SILVER 12 [hp_X]/20 mL; PEUMUS BOLDUS LEAF 4 [hp_X]/20 mL; RICINUS COMMUNIS SEED 4 [hp_X]/20 mL; COMBRETUM MICRANTHUM LEAF 4 [hp_X]/20 mL; JATEORHIZA CALUMBA ROOT 4 [hp_X]/20 mL
INACTIVE INGREDIENTS: ALCOHOL; WATER

Unda 13

Active ingredients
Each drop contains:
Argentum metallicum (Silver) 12X
Boldo Leaf 4X

Combretum raimbaultii Leaf 4X
Jateorhiza palmata (Columbo) Root 4X
Ricinus communis (Castor bean) Seed 4X

Uses
For the temporary relief of symptoms associated with digestive upset.

Warnings
Stop use and ask a doctor if symptoms persist or worsen.

If pregnant or breastfeeding, ask a health professional before use.
Keep out of reach of children. In case of overdose, get medical help or contact
a Poison Control Center right away.

PREGNANCY OR BREAST FEEDING

If pregnant or breastfeeding, ask a health professional before use.

Keep out of reach of children.

OVERDOSAGE

In case of overdose, get medical help or contact a
Poison Control Center right away.

Stop use and ask a doctor if symptoms persist or worsen.

Inactive ingredients
Ethanol (beet), purified water

Other information
Do not use if seal is missing or broken.
Store in a cool, dry place.
Contents may not fill package in order to accommodate required labeling. Please rely on stated quantity.

Directions
Adults and adolescents (12 years and older)

Take 5 drops three times daily or as recommended by your healthcare practitioner.
Children (under 12 years)
Take under the direction of your healthcare practitioner.

Uses
For the temporary relief of symptoms associated with digestive upset.

Directions
Adults and adolescents (12 years and older)

Take 5 drops three times daily or as recommended by your healthcare practitioner.
Children (under 12 years)
Take under the direction of your healthcare practitioner.

PACKAGE LABEL

NDC 62106-1112-8

UNDA

numbered compounds

UNDA 13

Homeopathic Preparation

For the temporary relief of symptoms
associated with digestive upset.

Contains 40% Alcohol
0.7 fl oz (20 mL)